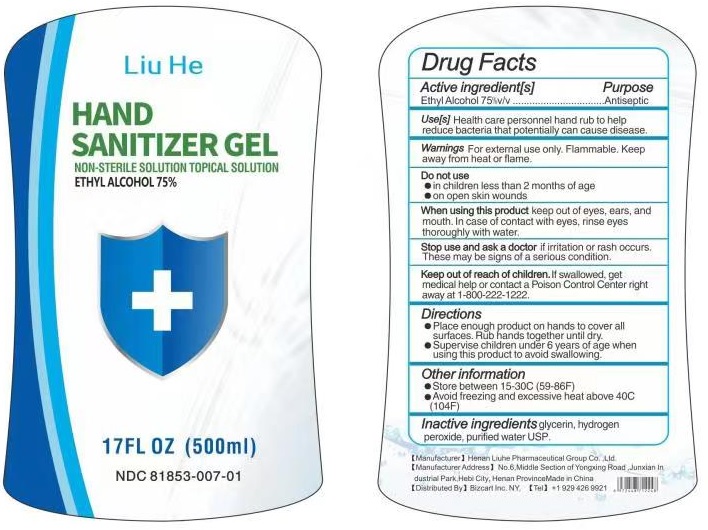 DRUG LABEL: Liu He HAND SANITIZER
NDC: 81853-007 | Form: GEL
Manufacturer: Henan Liuhe Pharmaceutical Group Co., Ltd.
Category: otc | Type: HUMAN OTC DRUG LABEL
Date: 20210511

ACTIVE INGREDIENTS: ALCOHOL 750 mg/1 mL
INACTIVE INGREDIENTS: GLYCERIN; HYDROGEN PEROXIDE; WATER

Liu He HAND SANITIZER GEL

Active ingredient[s]

Ethyl Alcohol 75% v/v

Purpose

Antiseptic

Use[s]

Health care personnel hand rub to help reduce bacteria that potentially can cause disease.

Warnings

For external use only. Flammable. Keep away from heat or flame.

Do not use
• in children less than 2 months of age
• on open skin wounds

When using this product keep out of eyes, ears, and mouth. In case of contact with eyes, rinse eyes thoroughly with water.

Stop use and ask a doctor if irritation or rash occurs. These may be signs of a serious condition.

Keep out of reach of children. If swallowed, get medical help or contact a Poison Control Center right away at 1-800-222-1222.

Directions

• Place enough product on hands to cover all surfaces. Rub hands together until dry.
• Supervise children under 6 years of age when using this product to avoid swallowing.

Other information

• Store between 15-30C (59-86F)
• Avoid freezing and excessive heat above 40C (104F)

Inactive ingredients

glycerin, hydrogen peroxide, purified water USP.

NON-STERILE SOLUTION TOPICAL SOLUTION

[Manufacturer] Henan Liuhe Pharmaceutical Group Co., Ltd.
[Manufacturer Address] No.6, Middle Section of Yongxing Road, Junxian Industrial Park,, Hebi City, Henan Province Made in China
[Distributed By] Bizcart Inc. NY. [Tel] +1 929 426 9921